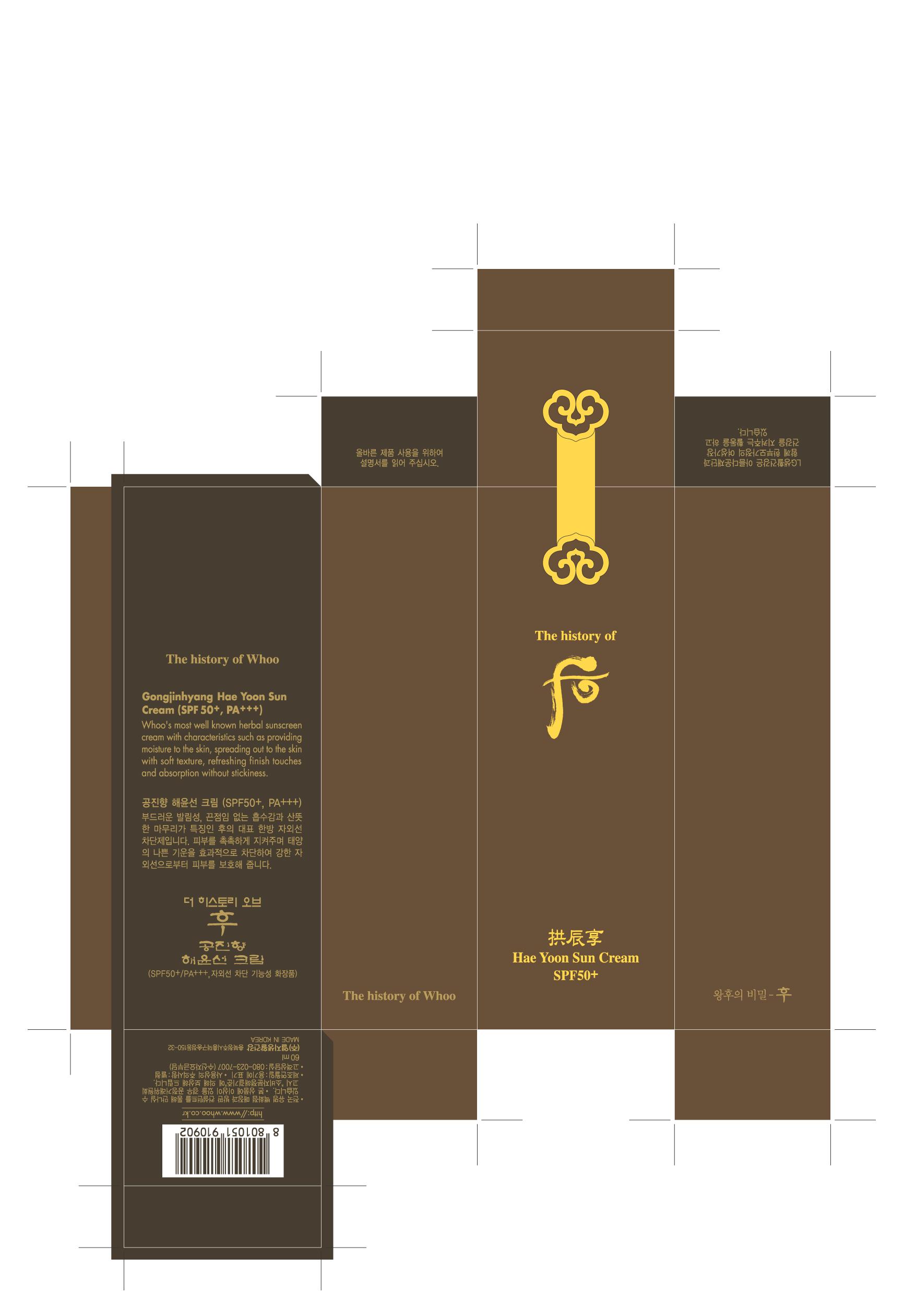 DRUG LABEL: THE HISTORY OF WHOO GONG JIN HYANG HAE YOON SUN
NDC: 53208-452 | Form: CREAM
Manufacturer: LG Household and Healthcare, Inc.
Category: otc | Type: HUMAN OTC DRUG LABEL
Date: 20100430

ACTIVE INGREDIENTS: BEMOTRIZINOL 0.8 mL/100 mL; OCTINOXATE 7 mL/100 mL
INACTIVE INGREDIENTS: WATER; BUTYLENE GLYCOL; CYCLOMETHICONE 5; DIPROPYLENE GLYCOL; POLYETHYLENE GLYCOL; GLYCERIN; CETOSTEARYL ALCOHOL; DOCOSANOL; PANTHENOL; PHENOXYETHANOL; METHYLPARABEN; XANTHAN GUM; PROPYLPARABEN; ETHYLPARABEN; ALPHA-TOCOPHEROL ACETATE; EDETATE TRISODIUM

DRUG FACTS

ACTIVE INGREDIENT

BEMOTRIZINOL 0.8mL/100mL

OCTINOXATE 7mL/100mL

WARNINGS AND PRECAUTIONS

For external use only

Keep out of reach of children. Is swallowed, get medical help or contact a Poison Control Center right away.

WHEN USING

Keep out of eyes. Rinse with water to remove.

Stop use if a rash or irritation develops and lasts.